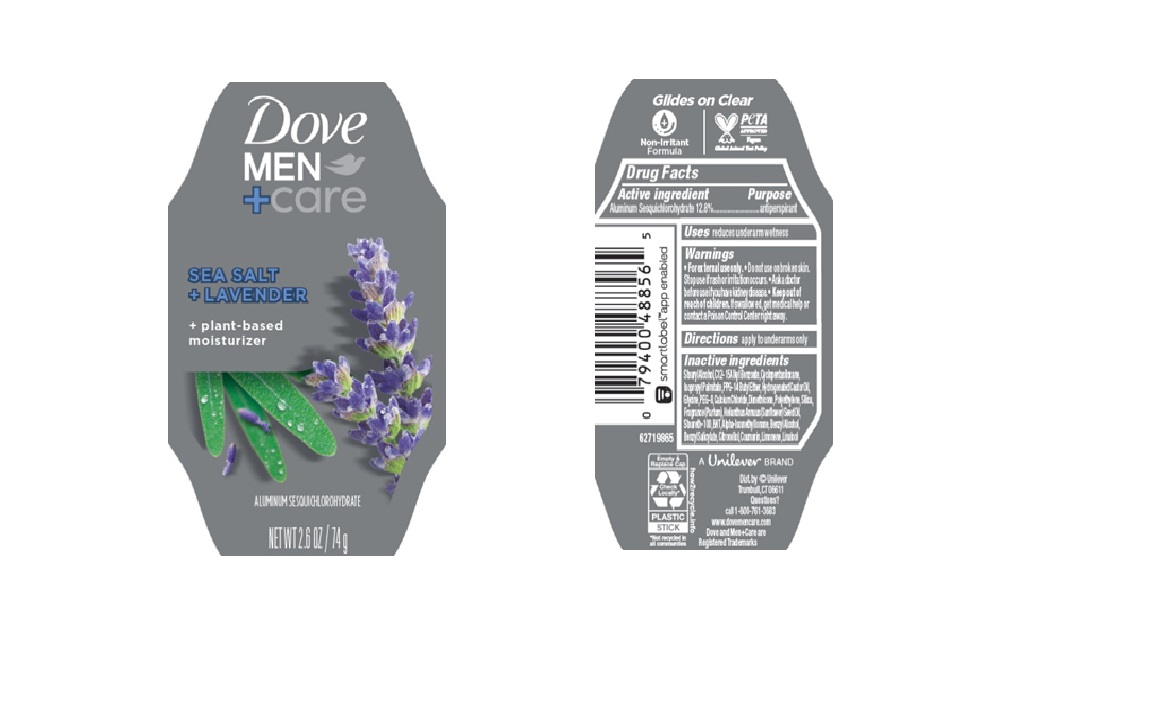 DRUG LABEL: Dove
NDC: 64942-2358 | Form: STICK
Manufacturer: Conopco d/b/a/ Unilever
Category: otc | Type: HUMAN OTC DRUG LABEL
Date: 20250331

ACTIVE INGREDIENTS: ALUMINUM SESQUICHLOROHYDRATE 12.8 g/100 g
INACTIVE INGREDIENTS: PEG-8; CALCIUM CHLORIDE; STEARYL ALCOHOL; PPG-14 BUTYL ETHER; CYCLOPENTASILOXANE; GLYCINE; SILICA; HYDROGENATED CASTOR OIL; DIMETHICONE; STEARETH-100; C12-15 ALKYL BENZOATE; COUMARIN; ISOPROPYL PALMITATE; LINALOOL, (+/-)-; POLYETHYLENE; BENZYL ALCOHOL; BENZYL SALICYLATE; CITRONELLOL; LIMONENE, (+)-; BHT; ALPHA-ISOMETHYL IONONE; HELIANTHUS ANNUUS (SUNFLOWER) SEED OIL

Dove Men + Care Sea Salt + Lavendar 72H Antiperspirant

DESCRIPTION

Dove Men + Care Sea Salt + Lavendar 72H Antiperspirant

ACTIVE INGREDIENT

Aluminum Sesquichlorohydrate (12.8%)

PURPOSE

antiperspirant

INDICATIONS AND USAGE

reduces underarm wetness

WARNINGS

For external use only.

Do not use on broken skin.

Ask a doctor before use if you have kidney disease.

Stop use if rash or irritation occurs.

• Keep out of reach of children.

If swallowed, get medical help or contact a Poison Control Center right away.

DOSAGE AND ADMINISTRATION

apply to underarms only

INACTIVE INGREDIENT

Stearyl Alcohol,C12 -15 Alkyl Benzoate,Cyclopentasiloxane, Isopropyl Palmitate,PPG -14 Butyl Ether, Hydrogenated Castor Oil, Glycine,PEG -8,Calcium Chloride,Dimethicone,Polyethylene,Silica, Fragrance (Parfum),Helianthus Annuus (Sunflower) Seed Oil, Steareth-100,BHT,Alpha-IsomethylIonone,Benzyl Alcohol, Benzyl Salicylate,Citronellol,Coumarin,Limonene,Linalool

QUESTIONS

Call 1-800-761-3683